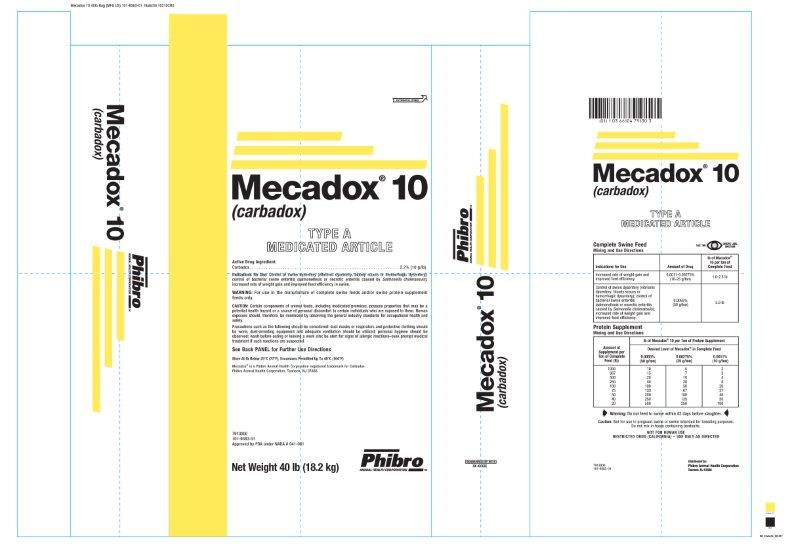 DRUG LABEL: Mecadox
NDC: 66104-0006 | Form: POWDER
Manufacturer: Phibro Animal Health
Category: animal | Type: OTC TYPE A MEDICATED ARTICLE ANIMAL DRUG LABEL
Date: 20231102

ACTIVE INGREDIENTS: CARBADOX 10 g/0.45 kg
INACTIVE INGREDIENTS: MINERAL OIL; CALCIUM PROPIONATE; SOYBEAN

Mecadox® 10
(carbadox)
TYPE A MEDICATED ARTICLE

Active Drug Ingredient:

Carbadox . . . . . . . . . . . . . . . . . . . . . . . . . . . . . . . . . . . . . . . . . . . . . . . . . . . . . . . . . 2.2% (10 g/lb)

Indications for Use:

Control of swine dysentery (vibrionic dysentery, bloody scours or hemorrhagic dysentery); control of bacterial swine enteritis (salmonellosis or necrotic enteritis caused by Salmonella choleraesuis); increased rate of weight gain and improved feed efficiency in swine.

WARNING:

For use in the manufacture of complete swine feeds and/or swine protein supplement feeds only.

CAUTION:

Certain components of animal feeds, including medicated premixes, possess properties that may be a potential health hazard or a source of personal discomfort to certain individuals who are exposed to them. Human exposure should, therefore, be minimized by observing the general industry standards for occupational health and safety.

Precautions such as the following should be considered: dust masks or respirators and protective clothing should be worn; dust-arresting equipment and adequate ventilation should be utilized; personal hygiene should be observed; wash before eating or leaving a work site; be alert for signs of allergic reactions–seek prompt medical treatment if such reactions are suspected.

Complete Swine Feed

Mixing and Use Directions

Indications for Use | Amount of Drug | lb of Mecadox® 10 per ton of Complete Feed
Increased rate of weight gain and improved feed efficiency | 0.0011-0.00275%; (10-25 g/ton) | 1.0-2.5 lb
Control of swine dysentery (vibrionic dysentery, bloody scours or hemorrhagic dysentery); control of bacterial swine enteritis (salmonellosis or necrotic enteritis caused by Salmonella choleraesuis); increased rate of weight gain and improved feed efficiency. | 0.0055%; (50 g/ton) | 5.0 lb

Protein Supplement

Mixing and Use Directions

Amount of Supplement per Ton of Complete Feed (lb) | lb of Mecadox® 10 per Ton of Protein Supplement
Amount of Supplement per Ton of Complete Feed (lb) | Desired Level of Mecadox® in Complete Feed
Amount of Supplement per Ton of Complete Feed (lb) | 0.0055%; (50 g/ton) | 0.00275%; (25 g/ton) | 0.0011%; (10 g/ton)
1000; 667; 500; 250; 100; 75; 50; 40; 20 | 10; 15; 20; 40; 100; 133; 200; 250; 500 | 5; 7; 10; 20; 50; 67; 100; 125; 250 | 2; 3; 4; 8; 20; 27; 40; 50; 100

Warning:

Do not feed to swine within 42 days before slaughter.

Caution: Not for use in pregnant swine or swine intended for breeding purposes.

Do not mix in feeds containing bentonite.

NOT FOR HUMAN USE

RESTRICTED DRUG (CALIFORNIA) – USE ONLY AS DIRECTED

Storage and Handling

Store At Or Below 25oC (77oF), Excursions Permitted Up To 40oC (104oF)

See Back PANEL for Further Use Directions

Mecadox® is a Phibro Animal Health Corporation registered trademark for Carbadox

Phibro Animal Health Corporation, Teaneck, NJ 07666.

Net Weight 40 lb (18.2 kg)

7913000

101-9383-01

Approved by FDA under NADA # 041-061

Mecadox 10